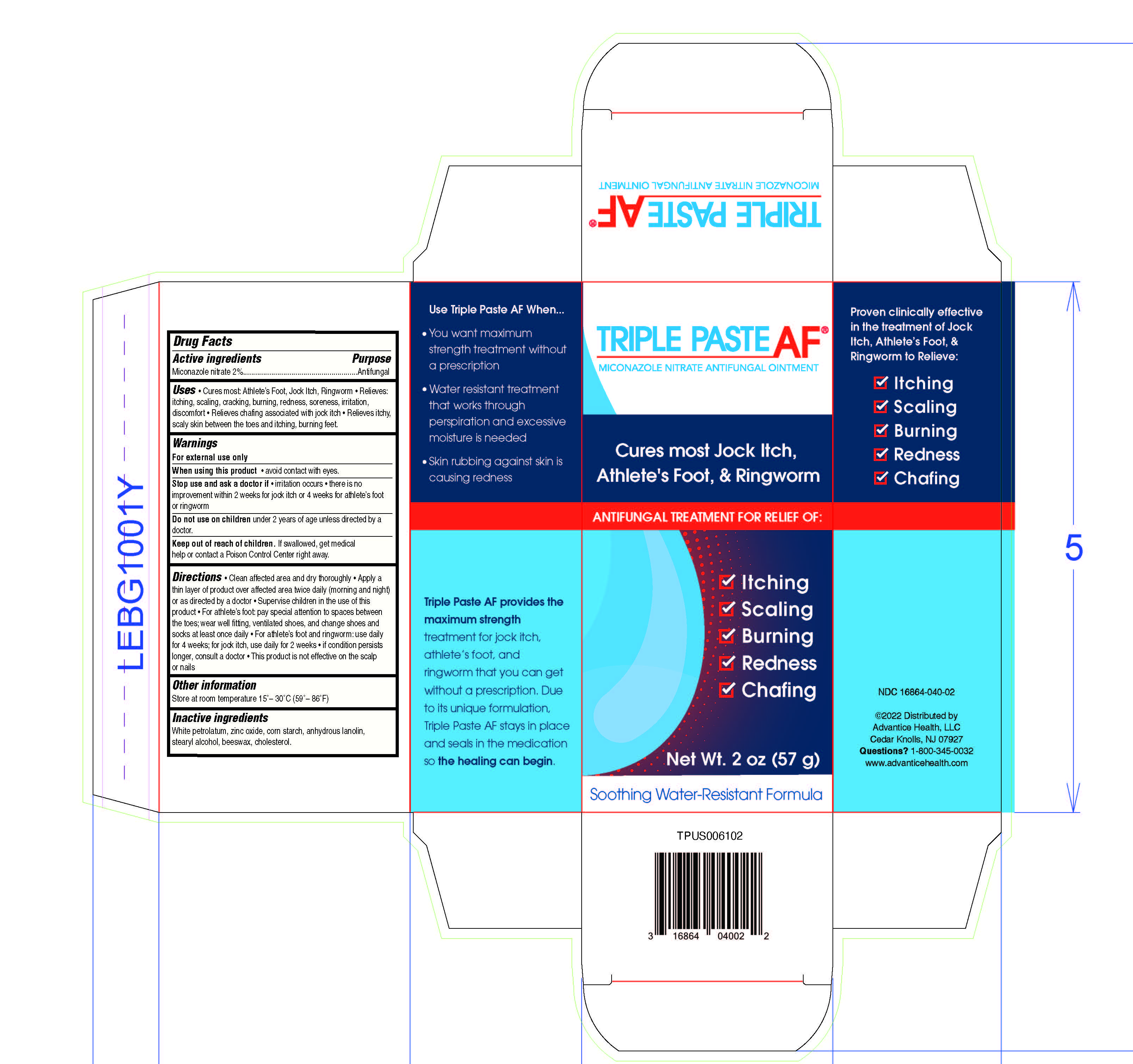 DRUG LABEL: Triple Antifungal
NDC: 16864-040 | Form: OINTMENT
Manufacturer: Advantice Health, LLC
Category: otc | Type: HUMAN OTC DRUG LABEL
Date: 20241212

ACTIVE INGREDIENTS: MICONAZOLE NITRATE 2 g/100 g
INACTIVE INGREDIENTS: WHITE PETROLATUM; STARCH, CORN; LANOLIN; STEARYL ALCOHOL; YELLOW WAX; LEVOMENOL; CHOLESTEROL; WATER; GLYCERIN; OAT

Triple Paste Antifungal Ointment

Drug Facts

Active ingredient

Miconazole nitrate 2%

Purpose

Antifungal

Uses

- For the treatment of superficial skin infections caused by yeast (Candida albicans)
- Relieves discomfort, irrit.ation, redness and chafing associated with jock itch
- Cures most jock itch (tinea cruris)

Warnings

For external use only

When using this productavoid contact with the eyes.

Stop use and ask a doctor if

- irritation occurs
- there is no improvement within 2 weeks

Do not use on childrenunder 2 years of age unless directed by a doctor.

Keep out of reach of children.

If swallowed, get medical help or contact a Poison Control Center right away.

Directions

- Clean affected area and dry thoroughly
- Apply a thin layer of product over affected area twice daily (morning and night) or as directed by a doctor
- Supervise children in the use of this product
- Use daily for 2 weeks; If condition persists longer, consult a doctor
- This product is not effective on the scalp or nails

Other information

Store at room temperature 15°– 30°C (59°– 86°F)

Inactive ingredients

White petrolatum, zinc oxide, corn starch, anhydrous lanolin, stearyl alcohol, beeswax, cholesterol.

Questions?

1-800-345-0032

Distributed by Advantice Health, LLC
Bridgewater, NJ 08807

PRINCIPAL DISPLAY PANEL - 56.7 g Tube Carton

Triple Paste AF®

2% MICONAZOLE NITRATE ANTIFUNGAL OINTMENT

- Relieves burning, redness,
  irritation and discomfort
- Unique, soothing,
  water-resistant formula
- Lubricates skin to heal
  and prevent chafing

Help is on the way...

Net Wt. 2 oz (56.7 g)